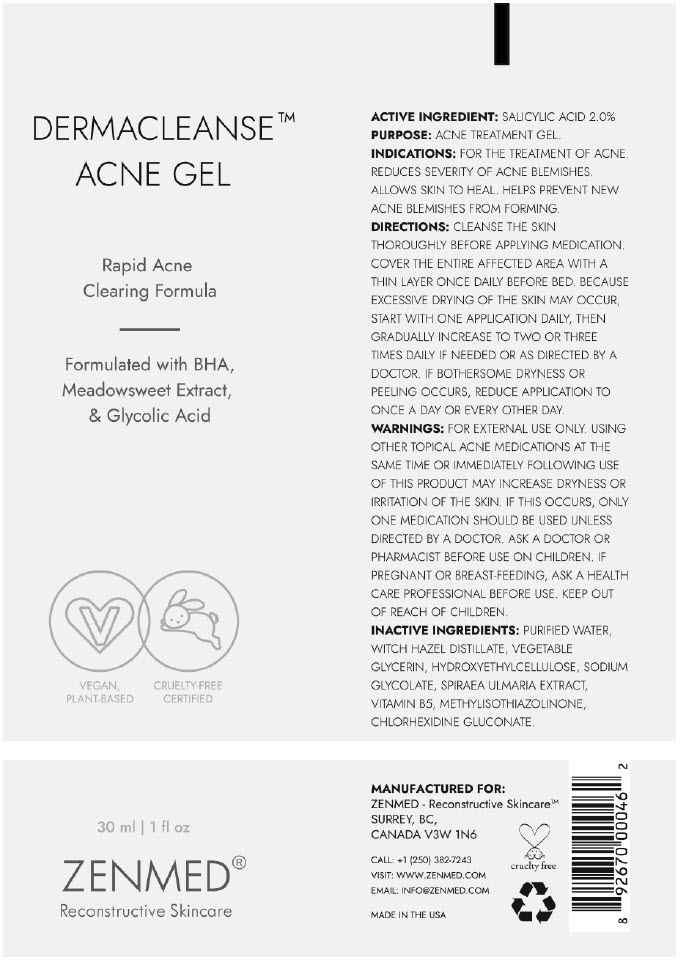 DRUG LABEL: DERMACLEANSE
NDC: 83313-0004 | Form: GEL
Manufacturer: ZENMED Raging Creations Ltd.
Category: otc | Type: HUMAN OTC DRUG LABEL
Date: 20240401

ACTIVE INGREDIENTS: SALICYLIC ACID 0.02 g/1 mL
INACTIVE INGREDIENTS: WATER; HAMAMELIS VIRGINIANA TOP WATER; HYDROXYETHYL CELLULOSE, UNSPECIFIED; SODIUM GLYCOLATE; FILIPENDULA ULMARIA FLOWER; PANTOTHENIC ACID; METHYLISOTHIAZOLINONE; CHLORHEXIDINE GLUCONATE

DERMACLEANSE™

ACTIVE INGREDIENT

SALICYLIC ACID 2.0%

PURPOSE

ACNE TREATMENT GEL.

INDICATIONS

FOR THE TREATMENT OF ACNE. REDUCES SEVERITY OF ACNE BLEMISHES. ALLOWS SKIN TO HEAL. HELPS PREVENT NEW ACNE BLEMISHES FROM FORMING.

DIRECTIONS

CLENSE THE SKIN THOROUGHLY BEFORE APPLYING MEDICATION. COVER THE ENTIRE AFFECTED AREA WITH A THIN LAYER ONCE DAILY BEFORE BED. BECAUSE EXCESSIVE DRYING OF THE SKIN MAY OCCUR, START WITH ONE APPLICATION DAILY, THEN GRADUALLY INCREASE TO TWO OR THREE TIMES DAILY IF NEEDED OR AS DIRECTED BY A DOCTOR. IF BOTHERSOME DRYNESS OR PEELING OCCURS, REDUCE APPLICATION TO ONCE A DAY OR EVERY OTHER DAY.

WARNINGS

FOR EXTERNAL USE ONLY. USING OTHER TOPICAL ACNE MEDICATIONS AT THE SAME TIME OR IMMEDIATELY FOLLOWING USE OF THIS PRODUCT MAY INCREASE DRYNESS OR IRRITATION OF THE SKIN. IF THIS OCCURS, ONLY ONE MEDICATION SHOULD BE USED UNLESS DIRECTED BY A DOCTOR. ASK A DOCTOR OR PHARMACIST BEFORE USE ON CHILDREN. IF PREGNANT OR BREAST-FEEDING, ASK A HEALTH CARE PROFESSIONAL BEFORE USE.

KEEP OUT OF REACH OF CHILDREN.

INACTIVE INGREDIENTS

PURIFIED WATER, WITCH HAZEL DISTILLATE, VEGETABLE GLYCERIN, HYDROXYETHYLCELLULOSE, SODIUM GLYCOLATE, SPIRAEA ULMARIA EXTRACT, VITAMIN B5, METHYLISOTHIAZOLINONE, CHLORHEXIDINE GLUCONATE.

PRINCIPAL DISPLAY PANEL - 30 ml Tube Label

DERMACLEANSE™
ACNE GEL

Rapid Acne
Clearing Formula

Formulated with BHA,
Meadowsweet Extract,
& Glycolic Acid

VEGAN,
PLANT-BASED

CRUELTY-FREE
CERTIFIED

30 ml | 1 fl oz

ZENMED®

Reconstructive Skincare